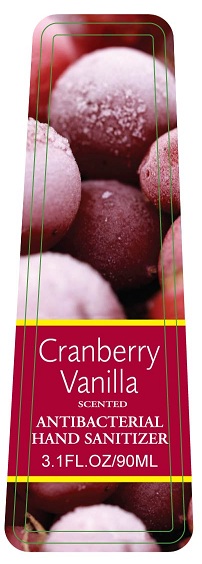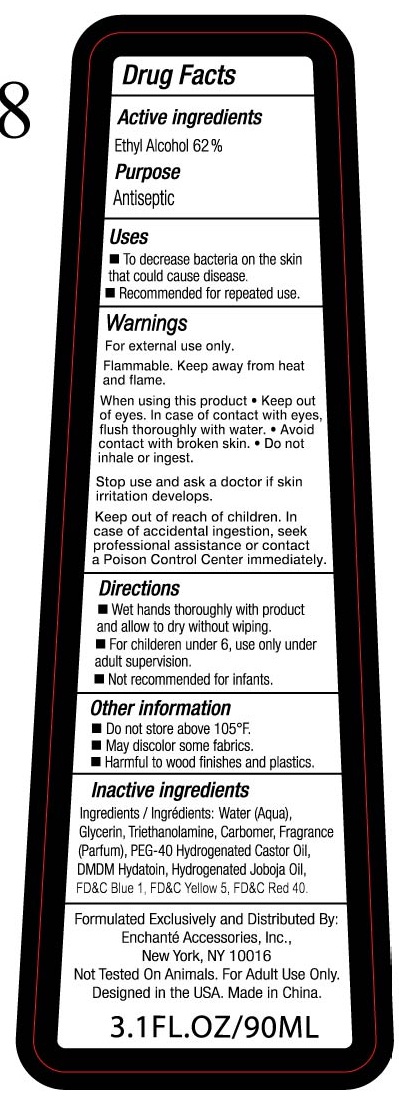 DRUG LABEL: Cranberry Vanilla Scented Antibacterial Hand Sanitizer
NDC: 50563-200 | Form: LIQUID
Manufacturer: Enchante Accessories
Category: otc | Type: HUMAN OTC DRUG LABEL
Date: 20100709

ACTIVE INGREDIENTS: ALCOHOL 62 mL/100 mL
INACTIVE INGREDIENTS: WATER; GLYCERIN; TROLAMINE; POLYOXYL 40 HYDROGENATED CASTOR OIL; DMDM HYDANTOIN; JOJOBA OIL

CRANBERRY VANILLA SCENTED ANTIBACTERIAL HAND SANITIZER

DRUG FACTS

Active Ingredients Purpose

Ethyl Alcohol 62% Antiseptic

Uses

To decrease bacteria on the skin that could cause disease

Recommended for repeated use.

Warnings:

For external use only-hands.

Flammable

Keep away from heat and flame.

When using this product

Keep out of eyes. In case of contact with eyes, flush thoroughly with water

Avoid contact with broken skin

Do not inhale or ingest

Stop use and ask a doctor if skin irritation develops.

Keep out of reach of children.

In case of accidental ingestion, seek professional assistance or contact a poison control center immediately

Directions

Wet hands thoroughly with product and allow to dry without wiping

For children under 6, use only under adult supervision

Not recommended for infants.

Other information

Do not store above 105 degrees F

May discolor some fabrics

Harmful to wood finishes and plastics.

Inactive ingredients

Ingredients/ingredients: water (aqua), glycerin, trethanolamine, carbomer, fragrance (parfum), PEG-40, hydrogenated castor oil, DMCM Hydantoin, hydrogenated jojoba oil, FD and C blue No1, FD and C yellow No 5, FD and C red40

Formulated exclusively and distributed by:
Enchante Accessories, Inc.
New York, NY 10016
Not Tested On Animals. For adult use only.
Designed in the USA
Made in China
3.1 fl oz/90 ml

PACKAGE LABEL

Cranberry Vanilla

scented

Antibacterial

Hand Sanitizer

3.1 fl. oz. / 90ml